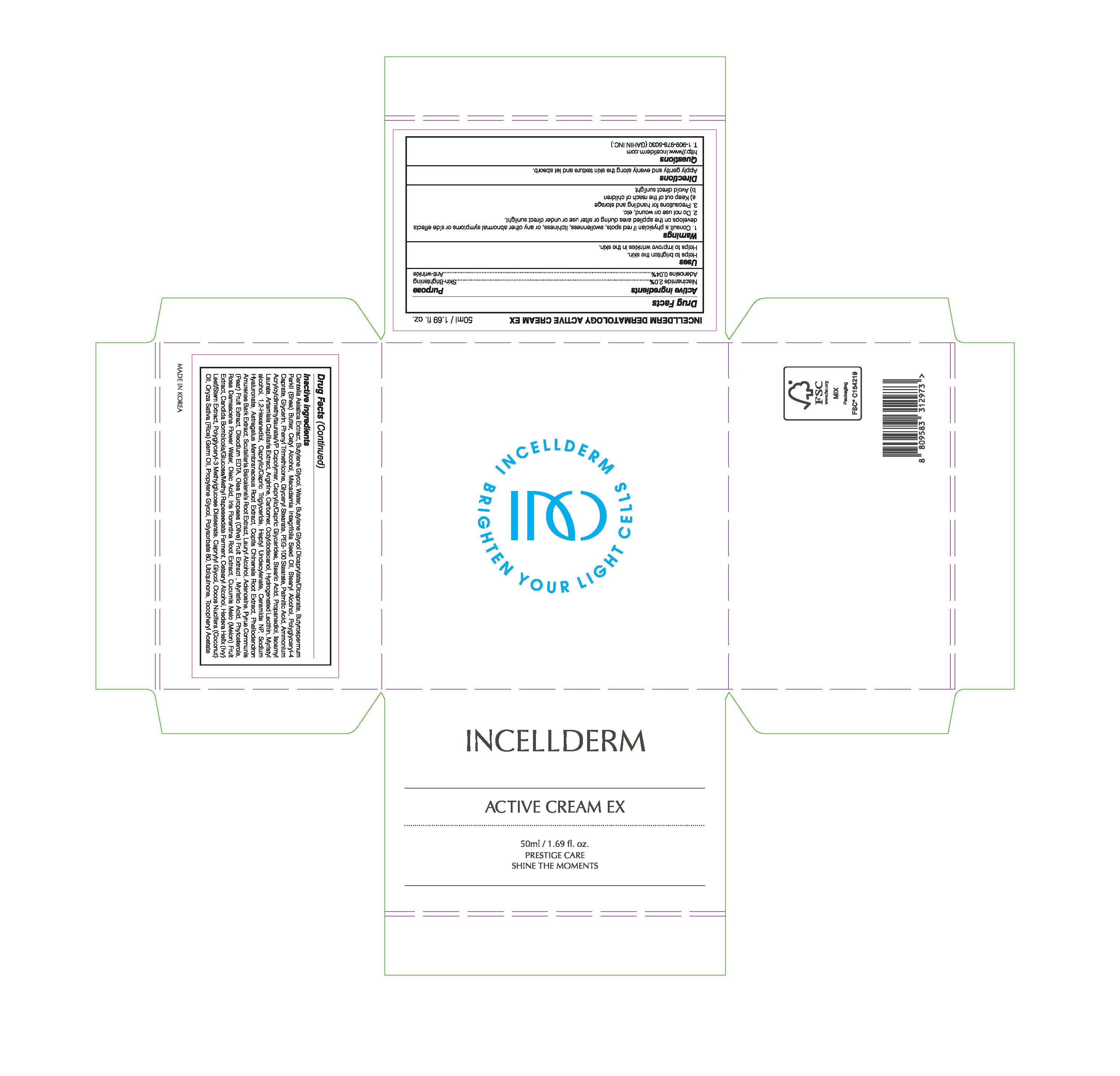 DRUG LABEL: INCELLDERM ACTIVE CREAMEX
NDC: 72650-102 | Form: CREAM
Manufacturer: Riman Korea Co., Ltd.
Category: otc | Type: HUMAN OTC DRUG LABEL
Date: 20210401

ACTIVE INGREDIENTS: NIACINAMIDE 2 g/100 mL; ADENOSINE 0.04 g/100 mL
INACTIVE INGREDIENTS: GLYCERIN; BUTYLENE GLYCOL

ACTIVE INGREDIENTS

Niacinamide, Adenosine

INACTIVE INGREDIENTS

Water, Caprylic/Capric Triglyceride, CetylEthylhexanoate, Titanium Dioxide, Propylene Glycol, Dimethicone, Hexyl Laurate, Cetyl PEG/PPG-10/1 Dimethicone, Magnesium Sulfate, Glycerin, Butylene Glycol, 1,2-Hexanediol, Panthenol, SorbitanSesquioleate, Glutathione, Hydrogenated Polyisobutene, Lavandula Angustifolia (Lavender) Oil, Centella Asiatica Leaf Extract , Hydroxyethylcellulose, Propanediol, Zinc Stearate, Microcrystalline Wax, Artemisia Capillaris Extract, Allantoin, Tocopheryl Acetate, Silica Dimethyl Silylate, Aluminum Hydroxide, Iron Oxides (CI 77492), Triethoxycaprylylsilane, Red Oxide (CI 77491), Iron Oxides (CI 77499), Citrus Aurantifolia (Lime) Fruit Extract, Disodium EDTA, Olea Europaea (Olive) Fruit Extract, Palmitoyl Tripeptide-5, Caprylyl Glycol, Palmitoyl Pentapeptide-4, Acetyl Hexapeptide-8, AnemarrhenaAsphodeloides Root Extract, Hydrogenated Lecithin, Glycine Soja (Soybean) Sterols, Hydroxydecyl Ubiquinone

PURPOSE

Helps to brighten the skin.

Helps to improve wrinkles in the skin.

WARNINGS

1. Consult a physician if red spots, swollenness, itchiness, or any other abnormal symptoms or side effects develops on the applied area during or after use or under direct sunlight.

2. Do not use on wound, etc.

3. Precautions for handling and storage

a) Keep out of the reach of children

b) Avoid direct sunlight

KEEP OUT OF REACH OF CHILDREN

Uses

Take a suitable amount and apply gently along the skin’s texture over your whole face

Directions

for external use only